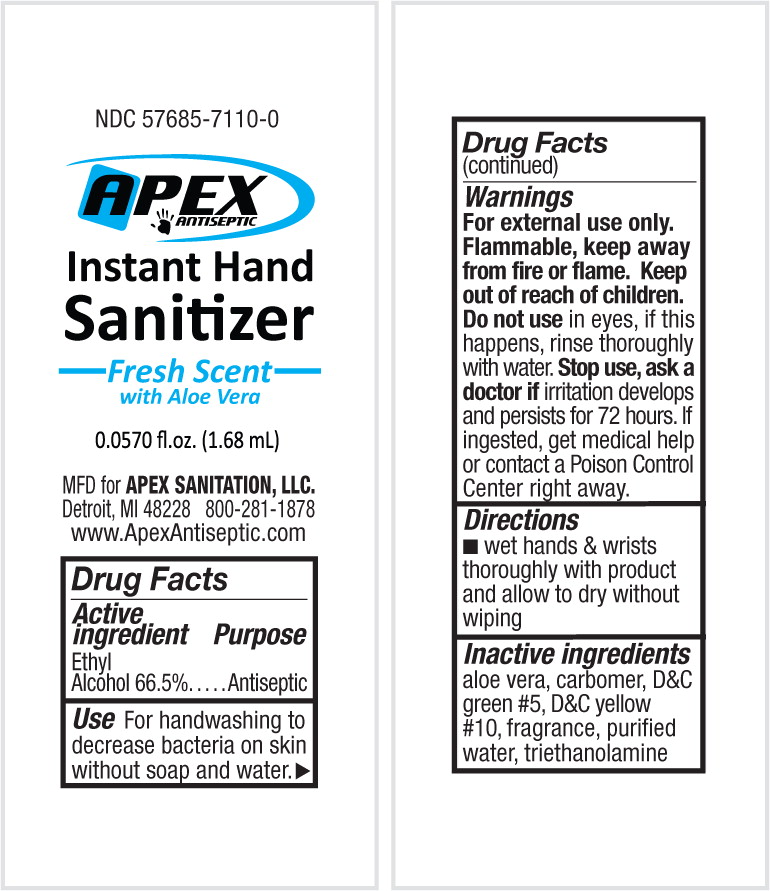 DRUG LABEL: Instant Hand Sanitizer
NDC: 57685-7110 | Form: GEL
Manufacturer: APEX Sanitation, LLC
Category: otc | Type: HUMAN OTC DRUG LABEL
Date: 20130327

ACTIVE INGREDIENTS: alcohol 540.26 g/1 L
INACTIVE INGREDIENTS: aloe; CARBOMER INTERPOLYMER TYPE A (ALLYL SUCROSE CROSSLINKED); d&c green no. 5; d&c yellow no. 10; water; trolamine

Drug Facts

Active ingredient

Ethyl Alcohol 66.5%

Purpose

Antiseptic

Use

For handwashing to decrease bacteria on skin without soap and water.

Warnings

For external use only. Flammable, keep away from fire or flame.

Do not use in eyes, if this happens, rinse thoroughly with water.

Stop use, ask doctor if irritation develops and persists for 72 hours. If ingested, get medical help or contact a Poison Control Center right away.

Directions

- wet hands & wrists thoroughly with product and allow to dry without wiping

Inactive ingredients

aloe vera, carbomer, D&C green # 5, D&C yellow # 10, fragrance, purified water, triethanolamine

PRINCIPAL DISPLAY PANEL – Pouch

NDC 57685-7110-0

APEX

ANTISEPTIC

Instant Hand

Sanitizer

Fresh Scent
with Aloe Vera

0.0570 fl.oz. (1.68 mL)

MFD for APEX SANITATION, LLC.

Detroit, MI 48228 800-281-1878

www.ApexAntiseptic.com